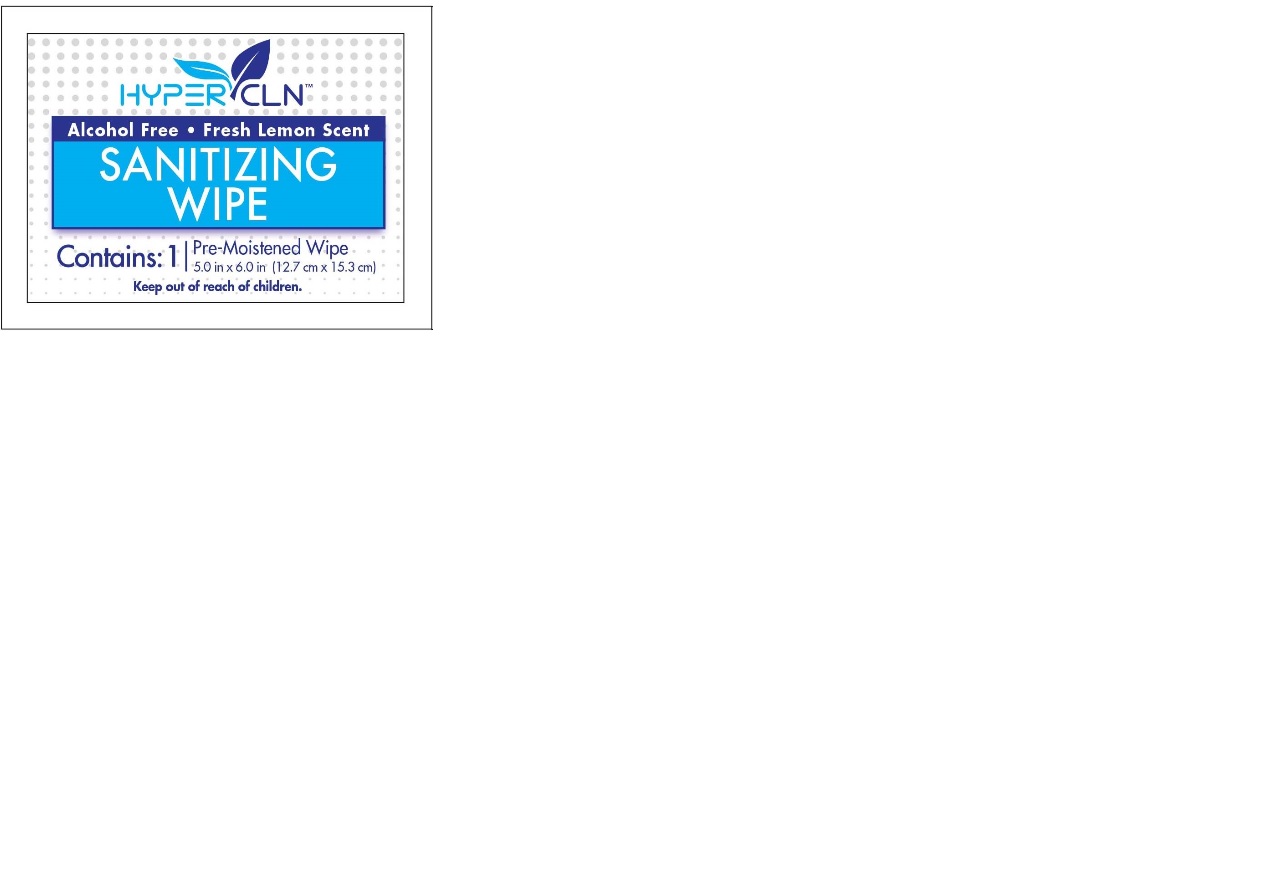 DRUG LABEL: Hypercln Sanitary Wipe
NDC: 78847-322 | Form: CLOTH
Manufacturer: Falcon Safety Products, Inc.
Category: otc | Type: HUMAN OTC DRUG LABEL
Date: 20200715

ACTIVE INGREDIENTS: BENZALKONIUM CHLORIDE 0.0013 1/1 1
INACTIVE INGREDIENTS: .ALPHA.-TOCOPHEROL ACETATE; CHAMOMILE; CITRONITRILE; EDETATE SODIUM; SODIUM BENZOATE; TETRAHYDROLINALOOL; EUCALYPTOL; 3,3'-DIHYDROXYDIPROPYL ETHER; ANHYDROUS CITRIC ACID; PANTHENOL; WATER; GLYCERIN; 3,7-DIMETHYL-1-OCTANOL; SODIUM HYDROXYMETHYLGLYCINATE; ALLANTOIN; ALOE VERA LEAF; POTASSIUM SORBATE; PEG-12 DIMETHICONE; DECYL GLUCOSIDE

Hypercln Sanitizing Wipes

Active ingredient

Benzalkonium chloride 0,13%

Purpose

Anti-bacterial

Indications

Hand sanitizer to help reduce bacteria on skin.

To use

To Use: open, unfold and apply. Sanitize hands or other affected area. Discard in trash after use. Do not flush.

Warnings

For external use only.

When using this product avoid contact with eyes. If in eyes, flush thoroughly with water.

Ask a doctor if

Stop and ask a doctor if:

• irritation develops. • condition persists for more than 72 hours.

Keep out of the reaach of children

If swallowed, get medical help or contact a Poison Control right away.

Inactive ingredients

Inactive Ingredients: Water, Decyl Glucoside, Glycerin, Sodium hydroxymethylglycinate, Citric Acid, PEG-12 Dimethicone, Fragrance, Sodium Benzoate, Potassium Sorbate, Allantoin, Tocopheryl Acetate, Aloe Barbadensis Leaf Water, Chamomilla Recutita (Matricaria) Flower Water, Panthenol, Tetrasodium EDTA, Benzyl Alcohol, Sodium Hydroxide